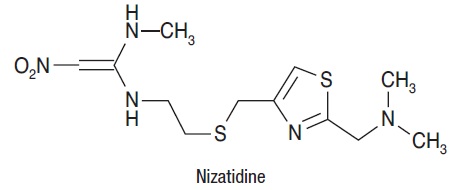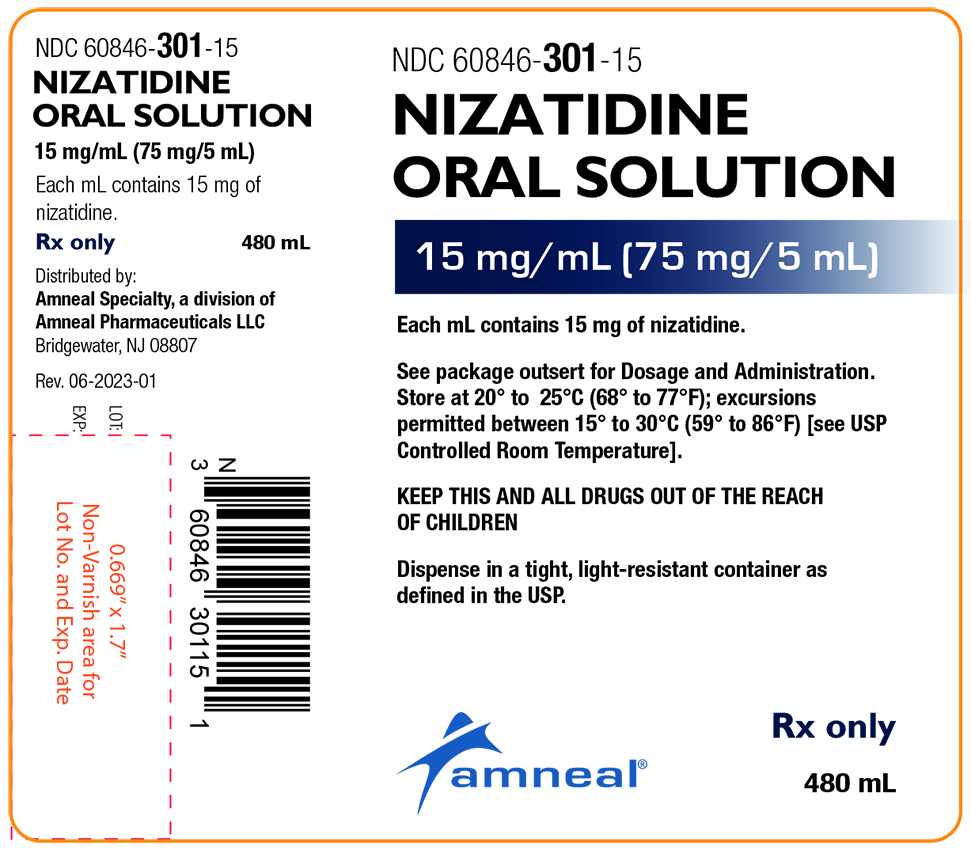 DRUG LABEL: NIZATIDINE
NDC: 60846-301 | Form: SOLUTION
Manufacturer: Amneal Pharmaceuticals LLC
Category: prescription | Type: HUMAN PRESCRIPTION DRUG LABEL
Date: 20241023

ACTIVE INGREDIENTS: NIZATIDINE 15 mg/1 mL
INACTIVE INGREDIENTS: ANHYDROUS CITRIC ACID; GLYCERIN; METHYLPARABEN; POVIDONE; PROPYLPARABEN; WATER; SACCHARIN SODIUM; SODIUM CHLORIDE; SODIUM CITRATE; SUCROSE; XANTHAN GUM

Nizatidine Oral Solution
15 mg/mL
Rx only

Description:

Nizatidine (USP) is a histamine H2-receptor antagonist. Chemically, it is N-[2-[[[2-[(dimethylamino)methyl]-4-thiazolyl]methyl]thio]ethyl]-N'-methyl-2-nitro-1,1-ethenediamine.

The structural formula is as follows:

Nizatidine has the empirical formula C12H21N5O2S2 representing a molecular weight of 331.47. It is an off-white to buff crystalline solid that is soluble in water. Nizatidine has a bitter taste and mild sulfur-like odor.

Nizatidine oral solution is a clear, pale-yellow, peppermint flavored solution and each 1 mL contains 15 mg of nizatidine. Nizatidine oral solution also contains the inactive ingredients anhydrous citric acid, glycerin, magnasweet, methylparaben, natural peppermint extract, povidone, propylparaben, purified water, saccharin sodium, sodium chloride, sodium citrate, sucrose and xanthan gum.

Clinical Pharmacology in Adults:

Nizatidine is a competitive, reversible inhibitor of histamine at the histamine H2-receptors, particularly those in the gastric parietal cells.

Antisecretory Activity—1. Effects on Acid Secretion: Nizatidine significantly inhibited nocturnal gastric acid secretion for up to 12 hours. Nizatidine also significantly inhibited gastric acid secretion stimulated by food, caffeine, betazole, and pentagastrin (Table 1).

Table 1. Effect of Oral Nizatidine on Gastric Acid Secretion
 | Time After Dose (h) | % Inhibition of Gastric Acid Output by Dose (mg)
 | Time After Dose (h) | 20 to 50 | 75 | 100 | 150 | 300
Nocturnal | Up to 10 | 57 | - | 73 | - | 90
Betazole | Up to 3 | - | 93 | - | 100 | 99
Pentagastrin | Up to 6 | - | 25 | - | 64 | 67
Meal | Up to 4 | 41 | 64 | - | 98 | 97
Caffeine | Up to 3 | - | 73 | - | 85 | 96

2. Effects on Other Gastrointestinal Secretions—Pepsin: Oral administration of 75 to 300 mg of nizatidine did not affect pepsin activity in gastric secretions. Total pepsin output was reduced in proportion to the reduced volume of gastric secretions.

Intrinsic Factor: Oral administration of 75 to 300 mg of nizatidine increased betazole-stimulated secretion of intrinsic factor.

Serum Gastrin Concentration: Nizatidine had no effect on basal serum gastrin concentration. No rebound of gastrin secretion was observed when food was ingested 12 hours after administration of nizatidine.

3. Other Pharmacologic Actions—

a. Hormones: Nizatidine was not shown to affect the serum concentrations of gonadotropins, prolactin, growth hormone, antidiuretic hormone, cortisol, triiodo-thyronine, thyroxin, testosterone, 5 α-dihydro-testosterone, androstenedione, or estradiol.

b. Nizatidine had no demonstrable antiandrogenic action.

4. Pharmacokinetics—The absolute oral bioavailability of nizatidine exceeds 70%. Peak plasma concentrations (700 to 1,800 mcg/L for a 150 mg dose and 1,400 to 3,600 mcg/L for a 300 mg dose) occur from 0.5 to 3 hours following the dose. Plasma concentrations 12 hours after administration are less than 10 mcg/L. The elimination half-life is 1 to 2 hours, plasma clearance is 40 to 60 L/h, and the volume of distribution is 0.8 to 1.5 L/kg. Because of the short half-life and rapid clearance of nizatidine, accumulation of the drug would not be expected in individuals with normal renal function who take either 300 mg once daily at bedtime or 150 mg twice daily. Nizatidine exhibits dose proportionality over the recommended dose range.

The oral bioavailability of nizatidine is unaffected by concomitant ingestion of the anticholinergic propantheline. Antacids consisting of aluminum and magnesium hydroxides with simethicone decrease the absorption of nizatidine by about 10%. With food, the AUC and Cmax increase by approximately 10%. In humans, less than 7% of an oral dose is metabolized as N2-monodesmethylnizatidine, an H2-receptor antagonist, which is the principal metabolite excreted in the urine. Other likely metabolites are the N2-oxide (less than 5% of the dose) and the S-oxide (less than 6% of the dose).

More than 90% of an orally administered dose of nizatidine is excreted in the urine within 12 hours. About 60% of an oral dose is excreted as unchanged drug. Renal clearance is about 500 mL/min, which indicates excretion by active tubular secretion. Less than 6% of an administered dose is eliminated in the feces.

Moderate to severe renal impairment significantly prolongs the half-life and decreases the clearance of nizatidine. In individuals who are functionally anephric, the half-life is 3.5 to 11 hours, and the plasma clearance is 7 to 14 L/h. To avoid accumulation of the drug in individuals with clinically significant renal impairment, the amount and/or frequency of doses of nizatidine should be reduced in proportion to the severity of dysfunction (see Dosage and Administration).

Approximately 35% of nizatidine is bound to plasma protein, mainly to α 1-acid glycoprotein. Warfarin, diazepam, acetaminophen, propantheline, phenobarbital, and propranolol did not affect plasma protein binding of nizatidine in vitro.

At a dose of 150 mg, the nizatidine oral solution (15 mg/mL) is bioequivalent to nizatidine capsules.

Clinical Pharmacology in Pediatric Patients:

Pharmacokinetics

Table 2 presents pharmacokinetic data of nizatidine administered orally to adolescents with gastroesophageal reflux (GER) and healthy adults. Pharmacokinetic parameters for adolescent patients ages 12 to 18 years are comparable to those obtained for adults.

Table 2. Pharmacokinetics of Oral Nizatidine
Age Range | Formulation | Dose | Cmax (ng/mL) | Tmax (h) | AUC 0-8 (ng∙h/mL) | CLF (L/h) | Vd F (L) | T 1/2 (h)
12 to 18 yr Adolescents with GER | Capsule | 150 mg SD | 1422.9 | 1.3 | 3764.2 | 41.0 | 71.4 | 1.2
12 to 18 yr Adolescents with GER |  | 150 mg SS | 1480.2 | 1.4 | 3776.1 | 41.1 | 74.2 | 1.3
Healthy Adults | Capsule | 150 mg SD | 1367.6 | 1.0 | 3703.1 | 41.9 | 83.4 | 1.4
Healthy Adults | Oral Solution | 150 mg SD | 1340.6 | 0.8 | 3610.9 | 43.0 | 86.4 | 1.4
Healthy Adults | Apple Juice | 150 mg SD | 762.8 | 1.3 | 2694.1 | 57.5 | 142.3 | 1.7
SD=single dose SS=steady-state

Administration of nizatidine capsules in apple juice results in 27% reduction of nizatidine bioavailability.

Pharmacodynamics

Pharmacodynamics of nizatidine was evaluated in 48 pediatric patients. These data suggest that gastric acid suppression is similar to that observed in adult studies (Table 3).

Table 3. Pharmacodynamics of Oral Nizatidine
Age | % Time pH>3 | % Time pH>4 | AUEC0-12h (pH∙h)
12 to 18 years | 57 | 42 | 41.4
Adults | 31 | 19 | 34.8

Clinical Trials (Adults)—1. Active Duodenal Ulcer: In multicenter, double-blind, placebo-controlled studies in the United States, endoscopically diagnosed duodenal ulcers healed more rapidly following administration of nizatidine, 300 mg h.s. or 150 mg b.i.d., than with placebo (Table 4). Lower doses, such as 100 mg h.s., had slightly lower effectiveness.

Table 4. Healing Response of Ulcers to Nizatidine
 | Nizatidine |  |  |  | Placebo
 | 300 mg h.s. |  | 150 mg bid
 | Number Entered | Healed/Evaluable | Number Entered | Healed/Evaluable | Number Entered | Healed/Evaluable
STUDY 1
Week 2 |  |  | 276 | 93/265 (35%)* | 279 | 55/260 (21%)
Week 4 |  |  |  | 198/259 (76%) |  | 95/243 (39%)
STUDY 2
Week 2 | 108 | 24/103 (23%)* | 106 | 27/101 (27%)* | 101 | 9/93 (10%)
Week 4 |  | 65/97 (67%)* |  | 66/97 (68%)* |  | 24/84 (29%)
STUDY 3
Week 2 | 92 | 22/90 (24%)† |  |  | 98 | 13/92 (14%)
Week 4 |  | 52/85 (61%)* |  |  |  | 29/88 (33%)
Week 8 |  | 68/83 (82%)* |  |  |  | 39/79 (49%)
*P<0.01 as compared with placebo. †P<0.05 as compared with placebo.

2. Maintenance of Healed Duodenal Ulcer: Treatment with a reduced dose of nizatidine has been shown to be effective as maintenance therapy following healing of active duodenal ulcers. In multi-center, double-blind, placebo-controlled studies conducted in the United States, 150 mg of nizatidine taken at bedtime resulted in a significantly lower incidence of duodenal ulcer recurrence in patients treated for up to 1 year (Table 5).

Table 5. Percentage of Ulcers Recurring by 3, 6, and 12 Months in Double-Blind Studies Conducted in the United States
Month | Nizatidine, 150 mg h.s. | Placebo
3 | 13% (28/208)* | 40% (82/204)
6 | 24% (45/188)* | 57% (106/187)
12 | 34% (57/166)* | 64% (112/175)
*P<0.001 as compared with placebo.

3. Gastroesophageal Reflux Disease (GERD): In 2 multicenter, double-blind, placebo-controlled clinical trials performed in the United States and Canada, nizatidine was more effective than placebo in improving endoscopically diagnosed esophagitis and in healing erosive and ulcerative esophagitis.

In patients with erosive or ulcerative esophagitis, 150 mg b.i.d. of nizatidine given to 88 patients compared with placebo in 98 patients in Study 1 yielded a higher healing rate at 3 weeks (16% vs 7%) and at 6 weeks (32% vs 16%, P<0.05). Of 99 patients on nizatidine and 94 patients on placebo, Study 2 at the same dosage yielded similar results at 6 weeks (21% vs 11%, P<0.05) and at 12 weeks (29% vs 13%, P<0.01).

In addition, relief of associated heartburn was greater in patients treated with nizatidine. Patients treated with nizatidine consumed fewer antacids than did patients treated with placebo.

4. Active Benign Gastric Ulcer: In a multicenter, double-blind, placebo-controlled study conducted in the United States and Canada, endoscopically diagnosed benign gastric ulcers healed significantly more rapidly following administration of nizatidine than of placebo (Table 6).

Table 6.
Week | Treatment | Healing Rate | vs. Placebo P-value*
4 | Nizatidine 300 mg h.s. | 52/153 (34%) | 0.342
 | Nizatidine 150 mg b.i.d | 65/151 (43%) | 0.022
 | Placebo | 48/151 (32%)
8 | Nizatidine 300 mg h.s | 99/153 (65%) | 0.011
 | Nizatidine 150 mg b.i.d | 105/151 (70%) | <0.001
 | Placebo | 78/151 (52%)
*P-values are one-sided, obtained by Chi-square test, and not adjusted for multiple comparisons.

In a multicenter, double-blind, comparator-controlled study in Europe, healing rates for patients receiving nizatidine (300 mg h.s. or 150 mg b.i.d.) were equivalent to rates for patients receiving a comparator drug, and statistically superior to historical placebo control rates.

Indications and Usage:

Nizatidine oral solution is indicated for up to 8 weeks for the treatment of active duodenal ulcer. In most patients, the ulcer will heal within 4 weeks.

Nizatidine oral solution is indicated for maintenance therapy for duodenal ulcer patients at a reduced dosage of 150 mg h.s. after healing of an active duodenal ulcer. The consequences of continuous therapy with nizatidine for longer than 1 year are not known.

Nizatidine oral solution is indicated for up to 12 weeks for the treatment of endoscopically diagnosed esophagitis, including erosive and ulcerative esophagitis, and associated heartburn due to GERD.

Nizatidine oral solution is indicated for up to 8 weeks for the treatment of active benign gastric ulcer. Before initiating therapy, care should be taken to exclude the possibility of malignant gastric ulceration.

In pediatric patients, nizatidine oral solution is indicated for ages 12 years and older. Nizatidine oral solution is indicated for up to 8 weeks for the treatment of endoscopically diagnosed esophagitis, including erosive and ulcerative esophagitis, and associated heartburn due to GERD.

Contraindication:

Nizatidine oral solution is contraindicated in patients with known hypersensitivity to the drug. Because cross-sensitivity in this class of compounds has been observed, H2-receptor antagonists, including nizatidine, should not be administered to patients with a history of hypersensitivity to other H2-receptor antagonists.

Precautions:

General—

1. Symptomatic response to nizatidine therapy does not preclude the presence of gastric malignancy.

2. Because nizatidine is excreted primarily by the kidney, dosage should be reduced in patients with moderate to severe renal insufficiency (see Dosage and Administration).

3. Pharmacokinetic studies in patients with hepatorenal syndrome have not been done. Part of the dose of nizatidine is metabolized in the liver. In patients with normal renal function and uncomplicated hepatic dysfunction, the disposition of nizatidine is similar to that in normal subjects.

Laboratory Tests—False-positive tests for urobilinogen with Multistix® may occur during therapy with nizatidine.

Drug Interactions—No interactions have been observed between nizatidine and theophylline, chlordiazepoxide, lorazepam, lidocaine, phenytoin, and warfarin. Nizatidine does not inhibit the cytochrome P-450-linked drug-metabolizing enzyme system; therefore, drug interactions mediated by inhibition of hepatic metabolism are not expected to occur. In patients given very high doses (3,900 mg) of aspirin daily, increases in serum salicylate levels were seen when nizatidine, 150 mg b.i.d., was administered concurrently.

Carcinogenesis, Mutagenesis, Impairment of Fertility—A 2-year oral carcinogenicity study in rats with doses as high as 500 mg/kg/day (about 13 times the recommended human dose based on body surface area) showed no evidence of a carcinogenic effect. There was a dose-related increase in the density of enterochromaffin-like (ECL) cells in the gastric oxyntic mucosa. In a 2-year study in mice, there was no evidence of a carcinogenic effect in male mice; although hyperplastic nodules of the liver were increased in the high-dose males as compared with placebo. Female mice given the high dose of nizatidine (2,000 mg/kg/day, about 27 times the recommended human dose based on body surface area) showed marginally statistically significant increases in hepatic carcinoma and hepatic nodular hyperplasia with no numerical increase seen in any of the other dose groups. The rate of hepatic carcinoma in the high-dose animals was within the historical control limits seen for the strain of mice used. The female mice were given a dose larger than the maximum tolerated dose, as indicated by excessive (30%) weight decrement as compared with concurrent controls and evidence of mild liver injury (transaminase elevations). The occurrence of a marginal finding at high dose only in animals given an excessive and somewhat hepatotoxic dose, with no evidence of a carcinogenic effect in rats, male mice, and female mice (given up to 360 mg/kg/day, about 5 times the recommended human dose based on body surface area), and a negative mutagenicity battery are not considered evidence of a carcinogenic potential for nizatidine.

Nizatidine was not mutagenic in a battery of tests performed to evaluate its potential genetic toxicity, including bacterial mutation tests, unscheduled DNA synthesis, sister chromatid exchange, mouse lymphoma assay, chromosome aberration tests, and a micronucleus test.

In a 2-generation, perinatal and postnatal fertility study in rats, doses of nizatidine up to 650 mg/kg/day (about 17.5 times the recommended human dose based on body surface area) produced no adverse effects on the reproductive performance of parental animals or their progeny.

Pregnancy—Teratogenic Effects—Pregnancy Category B—Oral reproduction studies in pregnant rats at doses up to 1500 mg/kg/day (about 40.5 times the recommended human dose based on body surface area) and in pregnant rabbits at doses up to 275 mg/kg/day (about 14.6 times the recommended human dose based on body surface area) have revealed no evidence of impaired fertility or harm to the fetus due to nizatidine. There are, however, no adequate and well-controlled studies in pregnant women. Because animal reproduction studies are not always predictive of human response, this drug should be used during pregnancy only if clearly needed.

Nursing Mothers—Studies conducted in lactating women have shown that 0.1% of the administered oral dose of nizatidine is secreted in human milk in proportion to plasma concentrations. Because of the growth depression in pups reared by lactating rats treated with nizatidine, a decision should be made whether to discontinue nursing or discontinue the drug, taking into account the importance of the drug to the mother.

Pediatric Use—Effectiveness in pediatric patients <12 years of age has not been established.

Use of nizatidine in pediatric patients from 12 to 18 years of age is supported by evidence from published pediatric literature, adequate and well-controlled published studies in adults, and by the following adequate and well-controlled studies in pediatric patients: (see Dosage and Administration)

Clinical Trials (Pediatric). In randomized studies, nizatidine was administered to pediatric patients for up to eight weeks, using age appropriate formulations. A total of 230 pediatric patients from 2 to 18 years of age were administered nizatidine at a dose of either 2.5 mg/kg b.i.d, or 5.0 mg/kg b.i.d, (patients 12 years and under) or 150 mg b.i.d (12 to 18 years). Patients were required to have either symptomatic, clinically suspected or endoscopically diagnosed GERD with age-relevant symptoms. In patients 2 to 18 years of age, nizatidine was found generally safe and well-tolerated. In these studies in patients 12 years and older, nizatidine was found to reduce the severity and frequency of GERD symptoms, improve physical well-being, and reduce the frequency of supplemental antacid consumption. No efficacy in pediatric patients <12 years of age has been established. Clinical studies in patients 2 to 12 years of age with GERD, demonstrated no difference in either symptom improvements or healing rates between nizatidine and placebo or between different doses of nizatidine.

Geriatric Use—Of the 955 patients in clinical studies who were treated with nizatidine, 337 (35.3%) were 65 and older. No overall differences in safety or effectiveness were observed between these and younger subjects. Other reported clinical experience has not identified differences in responses between the elderly and younger patients, but greater sensitivity of some older individuals cannot be ruled out.

This drug is known to be substantially excreted by the kidney, and the risk of toxic reactions to this drug may be greater in patients with impaired renal function. Because elderly patients are more likely to have decreased renal function, care should be taken in dose selection, and it may be useful to monitor renal function (see Dosage and Administration).

Adverse Reactions in Adults:

Worldwide, controlled clinical trials of nizatidine included over 6,000 patients given nizatidine in studies of varying durations. Placebo-controlled trials in the United States and Canada included over 2,600 patients given nizatidine and over 1,700 given placebo. Among the adverse events in these placebo-controlled trials, anemia (0.2% vs 0%) and urticaria (0.5% vs 0.1%) were significantly more common in the nizatidine group.

Incidence in Placebo-Controlled Clinical Trials in the United States and Canada—Table 7 lists adverse events that occurred at a frequency of 1% or more among nizatidine-treated patients who participated in placebo-controlled trials. The cited figures provide some basis for estimating the relative contribution of drug and non-drug factors to the side-effect incidence rate in the population studied.

Table 7. Incidence of Treatment-Emergent Adverse Events in Placebo-Controlled Clinical Trials in the United States and Canada
 | Percentage of Patients Reporting Event |  |  | Percentage of Patients Reporting Event
Body System/ Adverse Event* | Nizatidine (N=2,694) | Placebo (N=1,729) | Body System/ Adverse Event* | Nizatidine (N=2,694) | Placebo (N=1,729)
Body as a Whole |  |  | Nervous
Headache | 16.6 | 15.6 | Dizziness | 4.6 | 3.8
Pain | 4.2 | 3.8 | Insomnia | 2.7 | 3.4
Asthenia | 3.1 | 2.9 | Abnormal dreams | 1.9 | 1.9
Chest pain | 2.3 | 2.1 | Somnolence | 1.9 | 1.6
Infection | 1.7 | 1.1 | Anxiety | 1.8 | 1.4
Injury, accident | 1.2 | 0.9 | Nervousness | 1.1 | 0.8
Digestive |  |  | Respiratory
Diarrhea | 7.2 | 6.9 | Rhinitis | 9.8 | 9.6
Dry mouth | 1.4 | 1.3 | Pharyngitis | 3.3 | 3.1
Tooth disorder | 1.0 | 0.8 | Sinusitis | 2.4 | 2.1
Musculoskeletal |  |  | Cough, increased | 2.0 | 2.0
Myalgia | 1.7 | 1.5 | Skin and Appendages
 |  |  | Rash | 1.9 | 2.1
 |  |  | Pruritis | 1.7 | 1.3
 |  |  | Special Senses
 |  |  | Amblyopia | 1.0 | 0.9
*Events reported by at least 1% of nizatidine–treated patients are included.

A variety of less common events were also reported; it was not possible to determine whether these were caused by nizatidine.

Hepatic—Hepatocellular injury, evidenced by elevated liver enzyme tests (SGOT [AST], SGPT [ALT], or alkaline phosphatase), occurred in some patients and was possibly or probably related to nizatidine. In some cases, there was marked elevation of SGOT, SGPT enzymes (greater than 500 IU/L) and, in a single instance, SGPT was greater than 2,000 IU/L. The overall rate of occurrences of elevated liver enzymes and elevations to 3 times the upper limit of normal, however, did not significantly differ from the rate of liver enzyme abnormalities in placebo-treated patients. All abnormalities were reversible after discontinuation of nizatidine. Since market introduction, hepatitis and jaundice have been reported. Rare cases of cholestatic or mixed hepatocellular and cholestatic injury with jaundice have been reported with reversal of the abnormalities after discontinuation of nizatidine.

Cardiovascular—In clinical pharmacology studies, short episodes of asymptomatic ventricular tachycardia occurred in 2 individuals administered nizatidine and in 3 untreated subjects.

CNS—Rare cases of reversible mental confusion have been reported.

Endocrine—Clinical pharmacology studies and controlled clinical trials showed no evidence of antiandrogenic activity due to nizatidine. Impotence and decreased libido were reported with similar frequency by patients who received nizatidine and by those given placebo. Rare reports of gynecomastia occurred.

Hematologic—Anemia was reported significantly more frequently in nizatidine- than in placebo-treated patients. Fatal thrombocytopenia was reported in a patient who was treated with nizatidine and another H2-receptor antagonist. On previous occasions, this patient had experienced thrombocytopenia while taking other drugs. Rare cases of thrombocytopenic purpura have been reported.

Integumental—Sweating and urticaria were reported significantly more frequently in nizatidine- than in placebo-treated patients. Rash and exfoliative dermatitis were also reported. Vasculitis has been reported rarely.

Hypersensitivity—As with other H2-receptor antagonists, rare cases of anaphylaxis following administration of nizatidine have been reported. Rare episodes of hypersensitivity reactions (eg, bronchospasm, laryngeal edema, rash, and eosinophilia) have been reported.

Body as a Whole—Serum sickness-like reactions have occurred rarely in conjunction with nizatidine use.

Genitourinary—Reports of impotence have occurred.

Other—Hyperuricemia unassociated with gout or nephrolithiasis was reported. Eosinophilia, fever, and nausea related to nizatidine administration have been reported.

Adverse Reactions (Pediatric):

In controlled clinical trials in pediatric patients (age 2 to 18 years), nizatidine was found to be generally safe and well tolerated. The principal adverse experiences (> 5%) were pyrexia, nasopharyngitis, diarrhea, vomiting, irritability, nasal congestion and cough. Most adverse events were mild or moderate in severity. Mild elevations in serum transaminase (1 to 2 x ULN) were noted in some patients. One subject experienced a seizure by EEG diagnosis after taking nizatidine oral solution 2.5 mg/kg b.i.d. for 23 days. The adverse reactions reported for nizatidine may also occur with nizatidine oral solution.

Overdosage:

Overdoses of nizatidine have been reported rarely. The following is provided to serve as a guide should such an overdose be encountered.

Signs and Symptoms—There is little clinical experience with overdosage of nizatidine in humans. Test animals that received large doses of nizatidine have exhibited cholinergic-type effects, including lacrimation, salivation, emesis, miosis, and diarrhea. Single oral doses of 800 mg/kg in dogs and of 1,200 mg/kg in monkeys were not lethal. Intravenous median lethal doses in the rat and mouse were 301 mg/kg and 232 mg/kg respectively.

In the two 8-week pediatric exposure trials of nizatidine in 256 pediatric patients, there were no cases of deliberate overdosage. In one study of nizatidine 10 mg/kg/day, drug compliance rates up to 7.5% above 100% compliance were not associated with clinically significant adverse events.

Treatment—To obtain up-to-date information about the treatment of overdose, a good resource is your certified Regional Poison Control Center. Telephone numbers of certified Poison Control Centers are listed in the Physicians’ Desk Reference (PDR). In managing overdosage, consider the possibility of multiple drug overdoses, interaction among drugs, and unusual drug kinetics in your patient.

If overdosage occurs, use of activated charcoal, emesis, or lavage should be considered along with clinical monitoring and supportive therapy. The ability of hemodialysis to remove nizatidine from the body has not been conclusively demonstrated; however, due to its large volume of distribution, nizatidine is not expected to be efficiently removed from the body by this method.

Dosage and Administration:

Active Duodenal Ulcer —The recommended oral dosage for adults is 300 mg once daily at bedtime. An alternative dosage regimen is 150 mg twice daily.

Maintenance of Healed Duodenal Ulcer —The recommended oral dosage for adults is 150 mg once daily at bedtime.

Gastroesophageal Reflux Disease —The recommended oral dosage in adults for the treatment of erosions, ulcerations, and associated heartburn is 150 mg twice daily.

Active Benign Gastric Ulcer—The recommended oral dosage is 300 mg given either as 150 mg twice daily or 300 mg once daily at bedtime. Prior to treatment, care should be taken to exclude the possibility of malignant gastric ulceration.

Each mL of nizatidine oral solution contains 15 mg of nizatidine. In adults, nizatidine oral solution may be substituted for any of the above indications using equivalent doses of the oral solution.

Pediatric Dosing—Each mL of oral solution contains 15 mg of nizatidine. Nizatidine oral solution is indicated for pediatric patients 12 years of age or older. For pediatric patients 12 years of age and older, the dosage of nizatidine is 150 mg b.i.d. (2 tsp, b.i.d.)

The following dosage recommendations are provided:

Erosive Esophagitis—For pediatric patients 12 years or older, the dosage is 150 mg b.i.d. (300 mg/d). The maximum daily dose for nizatidine PO is 300 mg/d. The dosing duration may be up to eight weeks.

Gastroesophageal Reflux Disease— For pediatric patients 12 years or older, the dosage is 150 mg b.i.d. (300 mg/d). The maximum daily dose for nizatidine PO is 300 mg/d. The dosing duration may be up to eight weeks.

Dosage Adjustment for Patients With Moderate to Severe Renal Insufficiency—The dose for patients with renal dysfunction should be reduced as follows:

Active Duodenal Ulcer, GERD, and Benign Gastric Ulcer
Creatinine Clearance | Dose
20 to 50 mL/min | 150 mg daily
<20 mL/min | 150 mg every other day
Maintenance Therapy
Creatinine Clearance | Dose
20 to 50 mL/min | 150 mg every other day
<20 mL/min | 150 mg every 3 days

Some elderly patients may have creatinine clearances of less than 50 mL/min, and, based on pharmacokinetic data in patients with renal impairment, the dose for such patients should be reduced accordingly. The clinical effects of this dosage reduction in patients with renal failure have not been evaluated.

Based on the pharmacokinetic data in elderly patients with renal impairment, pediatric patients with creatinine clearances less than 50 mL/min, should have their dose of nizatidine reduced accordingly. The clinical effects of this dose reduction in pediatric patients with renal failure have not been evaluated.

How Supplied:

Nizatidine Oral Solution 15 mg/mL is a clear, pale-yellow, peppermint flavored solution, available as

Bottles of 480 mL – NDC 60846-301-15

Store at 20° to 25°C (68° to 77°F); excursions permitted between 15° to 30°C (59° to 86°F) [see USP Controlled Room Temperature].

Dispense contents with a child-resistant closure (as required) and in a tight, light-resistant container as defined in the USP.

KEEP THIS AND ALL DRUGS OUT OF THE REACH OF CHILDREN

Rx only

Distributed by:
Amneal Specialty, a division of Amneal Pharmaceuticals LLC
Bridgewater, NJ 08807

Rev. 02-2021-01